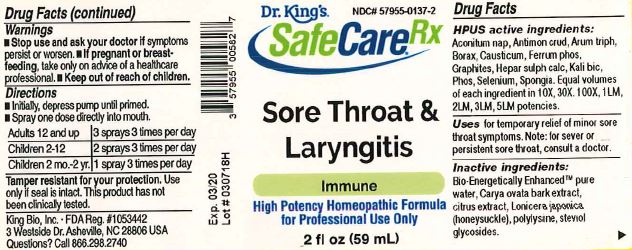 DRUG LABEL: Sore Throat and Laryngitis
NDC: 57955-0137 | Form: LIQUID
Manufacturer: King Bio Inc.
Category: homeopathic | Type: HUMAN OTC DRUG LABEL
Date: 20180614

ACTIVE INGREDIENTS: ACONITUM NAPELLUS 10 [hp_X]/59 mL; ANTIMONY TRISULFIDE 10 [hp_X]/59 mL; ARISAEMA TRIPHYLLUM ROOT 10 [hp_X]/59 mL; SODIUM BORATE 10 [hp_X]/59 mL; CAUSTICUM 10 [hp_X]/59 mL; FERROSOFERRIC PHOSPHATE 10 [hp_X]/59 mL; GRAPHITE 10 [hp_X]/59 mL; CALCIUM SULFIDE 10 [hp_X]/59 mL; POTASSIUM DICHROMATE 10 [hp_X]/59 mL; PHOSPHORUS 10 [hp_X]/59 mL; SELENIUM 10 [hp_X]/59 mL; SPONGIA OFFICINALIS SKELETON, ROASTED 10 [hp_X]/59 mL
INACTIVE INGREDIENTS: WATER; CARYA OVATA BARK; CITRUS BIOFLAVONOIDS; LONICERA JAPONICA FLOWER; POLYEPSILON-LYSINE (4000 MW); REBAUDIOSIDE A

Sore Throat and Laryngitis™

ACTIVE INGREDIENT

Drug Facts__________________________________________________________________________________________________________

HPUS active ingredients: Aconitum nap, Antimon crud, Arum triph, Borax, Causticum, Ferrum phos, Graphites, Hepar sulph calc, Kali bic, Phos, Selenium, Spongia. Equal volumes of each ingredient in 10X, 30X, 100X, 1LM, 2LM, 3LM, 5LM potencies.

INDICATIONS AND USAGE

Uses for temporary relief of minor sore throat symptoms. Note: for severe or persistent sore throat, consult a doctor.

Inactive Ingredients:

Bio-Energetically Enhanced™ pure water, Carya ovata bark extract, citrus extract, Lonicera japonica (honeysuckle), polylysine, steviol glycosides.

Warnings

- Stop use and ask your doctor if symptoms persist or worsen.
- If pregnant or breast-feeding, take only on advice of a healthcare professional.

- Keep out of reach of children.

Directions

- Initially, depress pump until primed.
- Spray one dose directly into mouth.
- Adults 12 and up: 3 sprays 3 times per day
- Children 2-12 years: 2 sprays 3 times per day
- Children 2mo.-2yr: 1 spray 3 times per day

OTHER SAFETY INFORMATION

Tamper resistant for your protection. Use only if safety seal is intact. This product has not been clinically tested.

PURPOSE

Uses for temporary relief of minor sore throat symptoms.